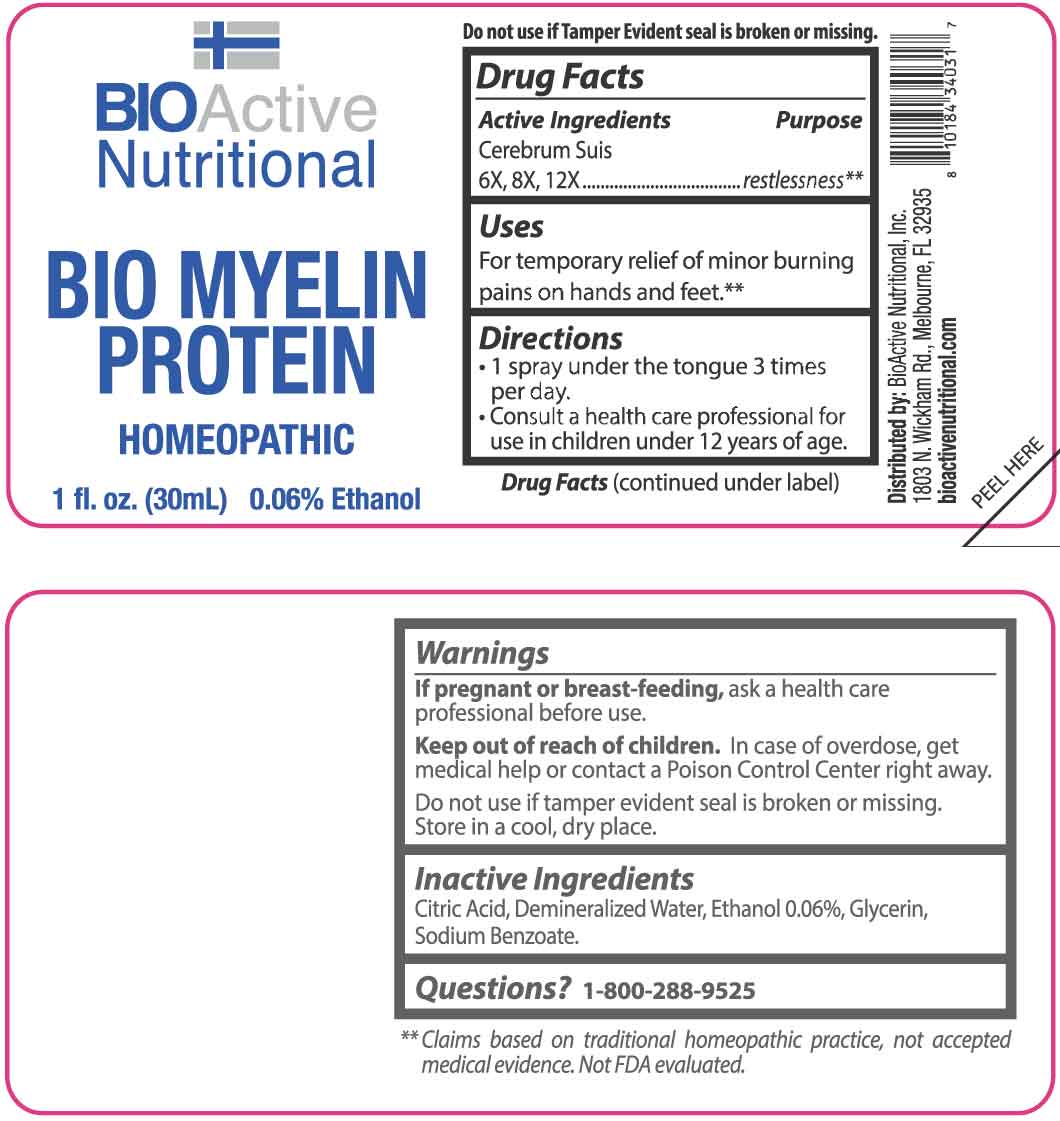 DRUG LABEL: Bio Myelin Protein
NDC: 43857-0443 | Form: SPRAY
Manufacturer: BioActive Nutritional, Inc.
Category: homeopathic | Type: HUMAN OTC DRUG LABEL
Date: 20251211

ACTIVE INGREDIENTS: SUS SCROFA CEREBRUM 6 [hp_X]/1 mL
INACTIVE INGREDIENTS: WATER; ALCOHOL; GLYCERIN; SODIUM BENZOATE; CITRIC ACID MONOHYDRATE

DRUG FACTS:

ACTIVE INGREDIENTS:

Cerebrum Suis 6X, 8X, 12X.

PURPOSE:

Cerebrum Suis - restlessness**

**Claims based on traditional homeopathic practice, not accepted medial evidence. Not FDA evaluated.

USES:

For temporary relief of minor burning pains on hands and feet.**

**Claims based on traditional homeopathic practice, not accepted medial evidence. Not FDA evaluated.

WARNINGS:

If pregnant or breast-feeding, ask a health care professional before use.

Keep out of reach of children. In case of overdose, get medical help or contact a Poison Control Center right away.

Do not use if tamper evident seal is broken or missing.

Store in a cool, dry place.

KEEP OUT OF REACH OF CHILDREN:

In case of overdose, get medical help or contact a Poison Control Center right away.

DIRECTIONS:

• 1 spray under the tongue 3 times per day.

• Consult a health care professional for use in children under 12 years of age.

INACTIVE INGREDIENTS:

Citric Acid, Demineralized Water, Ethanol 0.06%, Glycerin, Sodium Benzoate.

QUESTIONS:

Distributed by:

BioActive Nutritional, Inc.

1803 N. Wickham Rd.

Melbourne, FL 32935

bioactivenutritional.com

1-800-288-9525

PACKAGE LABEL DISPLAY:

BIOActive Nutritional

BIO MYELIN

PROTEIN

HOMEOPATHIC

1 fl. oz. (30 mL)